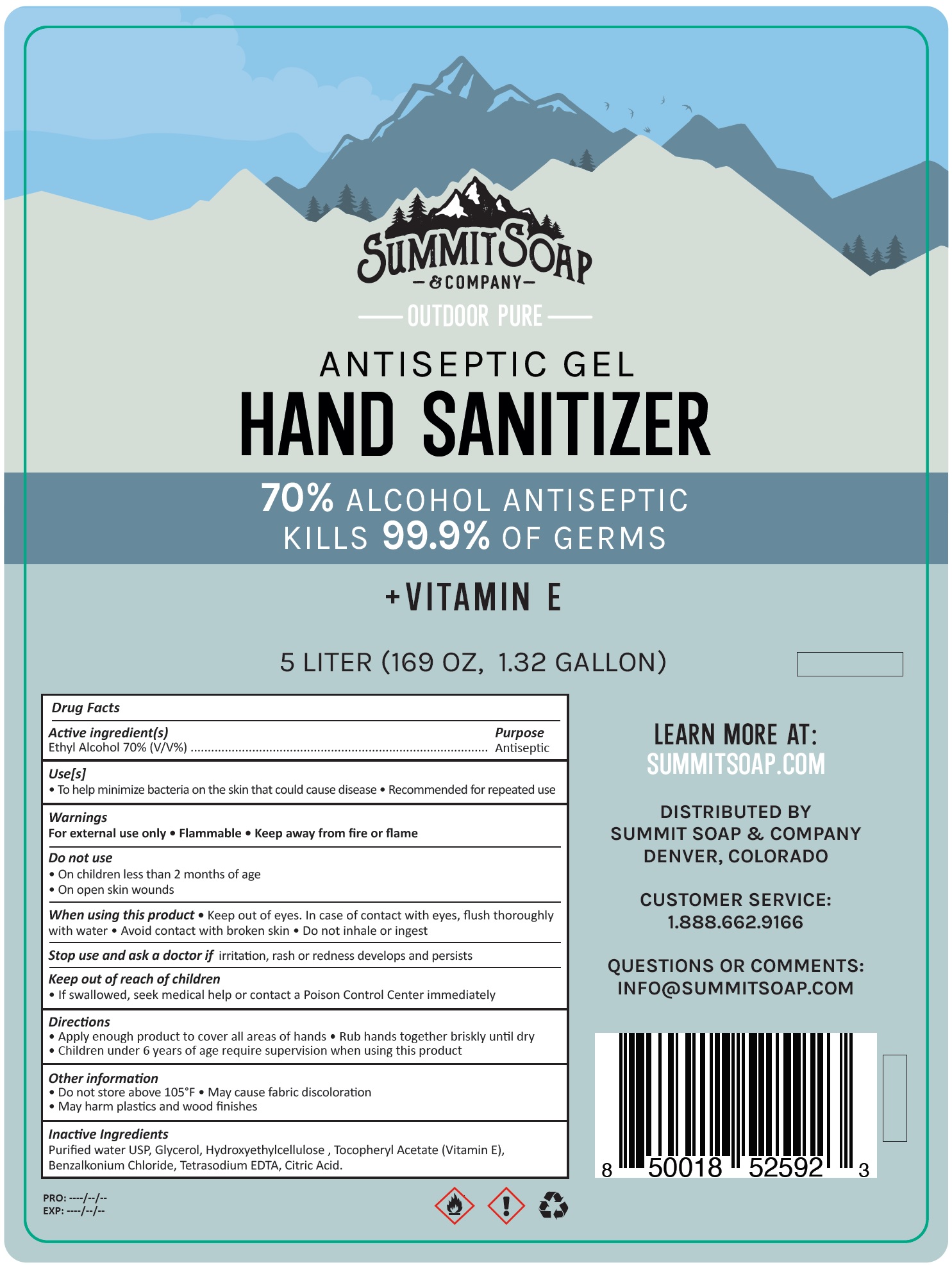 DRUG LABEL: Summit Hand Sanitizer
NDC: 79190-000 | Form: GEL
Manufacturer: IMO SOURCE (PTY) LTD
Category: otc | Type: HUMAN OTC DRUG LABEL
Date: 20200629

ACTIVE INGREDIENTS: ALCOHOL 0.7 mL/1 mL
INACTIVE INGREDIENTS: WATER; GLYCERIN; HYDROXYETHYL CELLULOSE, UNSPECIFIED; .ALPHA.-TOCOPHEROL ACETATE; BENZALKONIUM CHLORIDE; EDETATE SODIUM; CITRIC ACID MONOHYDRATE

Summit Soap Hand Sanitizer

Active ingredient(s)

Ethyl Alcohol 70% (V/V%)

Purpose

Antiseptic

Use[s]

- To help minimize bacteria on the skin that could cause disease
- Recommended for repeated use

Warnings

For external use only

• Flammable

• Keep away from fire or flame

Do not use

- On children less than 2 months of age
- On open skin wounds

When using this product

- Keep out of eyes. In case of contact with eyes, flush thoroughly with water
- Avoid contact with broken skin
- Do not inhale or ingest

Stop use and ask a doctor if

irritation, rash or redness develops and persists

Keep out of reach of children

- If swallowed, seek medical help or contact a Poison Control Center immediately

Directions

- Apply enough product to cover all areas of hands
- Rub hands together briskly until dry
- Children under 6 years of age require supervision when using this product

Other information

- Do not store above 105°F
- May cause fabric discoloration
- May harm plastics and wood finishes

Inactive Ingredients

Purified water USP, Glycerol, Hydroxyethylcellulose , Tocopheryl Acetate (Vitamin E), Benzalkonium Chloride, Tetrasodium EDTA, Citric Acid.